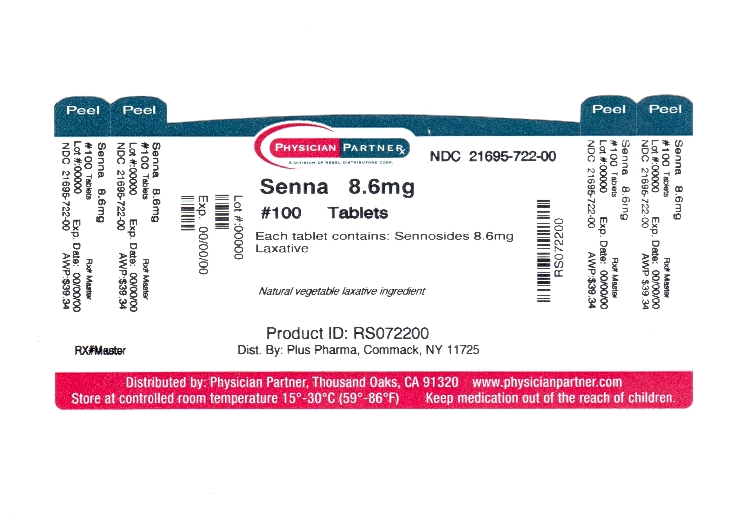 DRUG LABEL: Senna Plus
NDC: 21695-722 | Form: TABLET
Manufacturer: Rebel Distributors Corp
Category: otc | Type: HUMAN OTC DRUG LABEL
Date: 20110907

ACTIVE INGREDIENTS: SENNOSIDES A AND B 8.6 mg/1 1
INACTIVE INGREDIENTS: CROSCARMELLOSE SODIUM; ANHYDROUS DIBASIC CALCIUM PHOSPHATE; HYPROMELLOSES; MAGNESIUM SILICATE; MAGNESIUM STEARATE; CELLULOSE, MICROCRYSTALLINE; MINERAL OIL; POLYETHYLENE GLYCOL; SODIUM BENZOATE; STARCH, CORN; STEARIC ACID; TITANIUM DIOXIDE

Senna Plus Drug Facts

Active ingredient

Sennosides from Senna Concentrate 8.6mg

Docusate Sodium 50mg

Purpose

Laxative & Stool Softener

Uses

For the short term relief of constipation. Produces bowel movement in 6 to 12 hours.

Warnings

Do not use ° for longer than one week ° when abdominal pain, nausea or vomiting are present.

Ask a doctor or pharmacist before use if you have noticed a sudden change in bowel habits that lasts over a period of two weeks.

Stop use and ask a doctor if ° you have rectal bleeding ° you fail to have a bowel movement after use of this product, this may indicate a serious condition.

If pregnant or breast-feeding, ask a health care professional before use.

KEEP OUT OF REACH OF CHILDREN

In case of overdose, get medical help or contact a Poison Control Center right away.

Directions

° Take preferably at bedtime or as directed by a doctor ° if you do not have a comfortable bowel movement by the second day, increase dose by one table (do not exceed the maximum dosage) or decrease dose until you are comfortable.

Adults & children over 12 years: 2 tablets once a day (maximum dosage, 4 tablets twice a day)

Children 6 to under 12 years: 1 tablet once a day (maximum dosage, 2 tablets twice a day)

Children 2 to under 6 years: 1.2 tablet once a day (maximum dosage, 1 tablet twice a day)

Children under 2 years: do not use

Other Information

Store at room temperature, USP.

Inactive ingredients

Croscarmellose Sodium, Dicalcium Phosphate, FD&C Yellow No. 5, FD&C Yellow No. 6, Hypromellose, Magnesium Silicate, Magnesium Stearate, Microcrystalline Cellulose, Mineral Oil, Polyethylene Glycol, Sodium Benzoate, Starch, Stearic Acid and Titanium Dioxide.

Distributed by: Plus Pharma

Commack, NY 11725

Repackaged by: Rebel Distributors Corp

Thousand Oaks, CA 91320